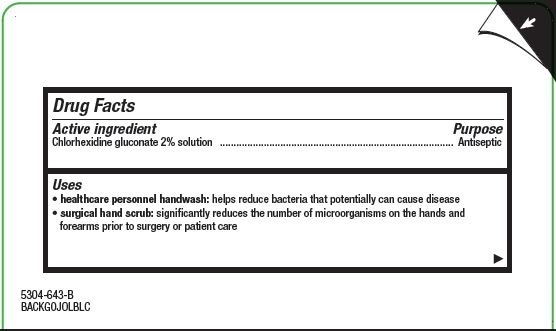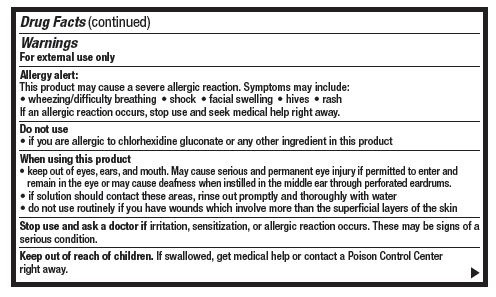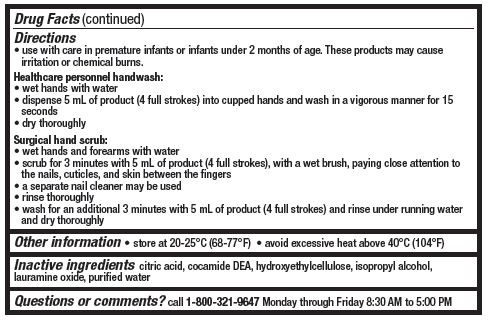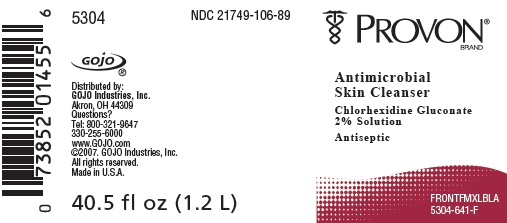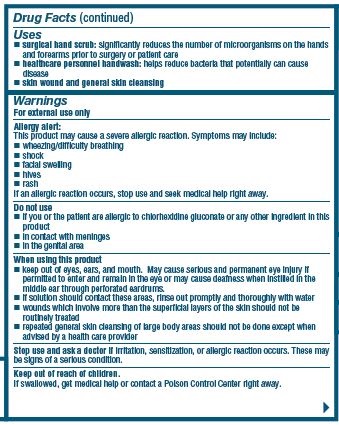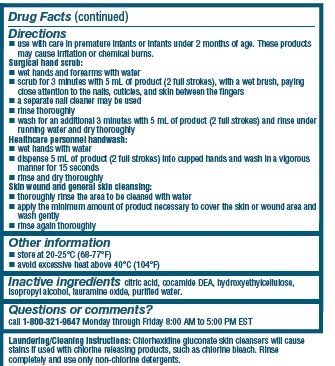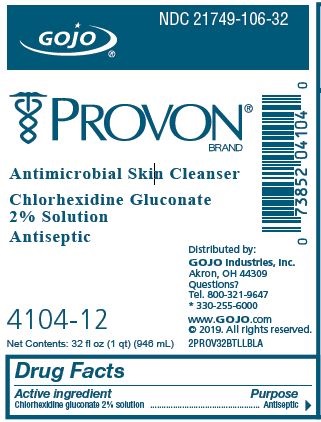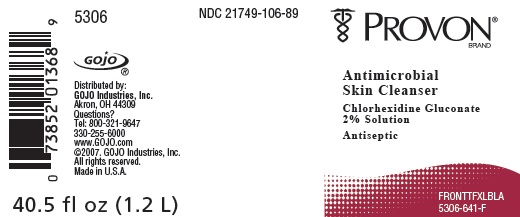 DRUG LABEL: Antimicrobial Skin Cleanser
NDC: 21749-106 | Form: LIQUID
Manufacturer: Gojo Industries, Inc.
Category: otc | Type: HUMAN OTC DRUG LABEL
Date: 20190618

ACTIVE INGREDIENTS: CHLORHEXIDINE GLUCONATE 20 mg/1 mL
INACTIVE INGREDIENTS: WATER; CITRIC ACID MONOHYDRATE; COCO DIETHANOLAMIDE; HYDROXYETHYL CELLULOSE (2000 MPA.S AT 1%); ISOPROPYL ALCOHOL; LAURAMINE OXIDE

GOJO FMX-TFX-Provon

Active ingredient

Chlorhexidine gluconate 2% solution

Purpose

Antiseptic

Uses

- healthcare personnel handwash: helps reduce bacteria that potentially can cause disease
- surgical hand scrub: significantly reduces the number of microorganisms on the hands and forearms prior to surgery or patient care

Warnings

For external use only

Allergy alert:

This product may cause a severe alleric reaction. Symptoms may include:

- wheezing/difficulty breathting
- shock
- facial swelling
- hives
- rash

If an allergic reaction occurs, stop use and seek medical help right away.

Do not use

if you are allergic to chlorhexidine gluconate or any other ingredient in this product

When using this product

- keep out of eyes, ears and mouth. May cause serious and permenant eye injury if permitted to enter and remain in the eye or may cause deafness when instilled through the middle ear through perforated eardrums.
- if solution should contact these areas, rinse out promptly and thoroughly with water
- do not use routinely if you have wounds which involve more than the superficial layers of the skin

Stop use and ask a doctor if

irritation, sensitization, or allergic reaction occurs. These may be signs of a serious condition.

Keep out of reach of children

If swallowed, get medical help or contact a Poison Control Center right away.

Directions

- use with care in premature infants under 2 months of age. These products may cause irritation or chemical burns.

Healthcare personnel handwash:

- wet hands with water
- dispense 5 mL of product (4 full strokes) into cupped hands and wash in a vigorous manner for 15 seconds
- dry thoroughly

Surgical hand scrub:

- wet hands and forearms with water
- scrub for 3 minutes with 5 mL of product (4 full strokes), with a wet brush, paying close attention to the nails, cuticles, and skin between the fingers
- a seperate nail cleaner may be used
- rinse thoroughly
- wash for an additional 3 minutes with 5 mL of product (4 full strokes) and rinse under running water and dry thoroughly

OTHER SAFETY INFORMATION

- store at 20-25ºC (68-77ºF)
- avoid excessive heat about 40ºC (104ºF)

Inactive ingredients

citric acid, cocamide DEA, hydroxyethylcellulose, isopropyl alcohol, lauramine oxide, purified water

Questions or comments?

call 1-800-321-9647 Monday through Friday 8:30 AM to 5:00 PM

PACKAGE LABEL

NDC 21749-106-89

Chlorhexidine Gluconate 2% Solution

Antimicrobial SKin Cleanser

Distributed by:

Gojo Industries, Inc.

Akron, OH 44309

330-255-6000

www.gojo.com

NDC 21749-106-89

Chlorhexidine Gluconate 2% Solution

Antimicrobial SKin Cleanser

Distributed by:

Gojo Industries, Inc.

Akron, OH 44309

330-255-6000

www.gojo.com

NDC 21749-106-32

PROVON BRAND

Antimicrobial Skin Cleanser

Chlorhexidine Gluconate

2% Solution

Antiseptic

Distributed by:

GOJO Industries, Inc.

Akron, OH 44309

Questions?

Tel. 800-321-9647

*330-255-6000

www.GOJO.com

©2018. All rights reserved.

2PROV32BTLLBL

4104-12

Net Contents: 32 fl oz (1qt) (946 mL)